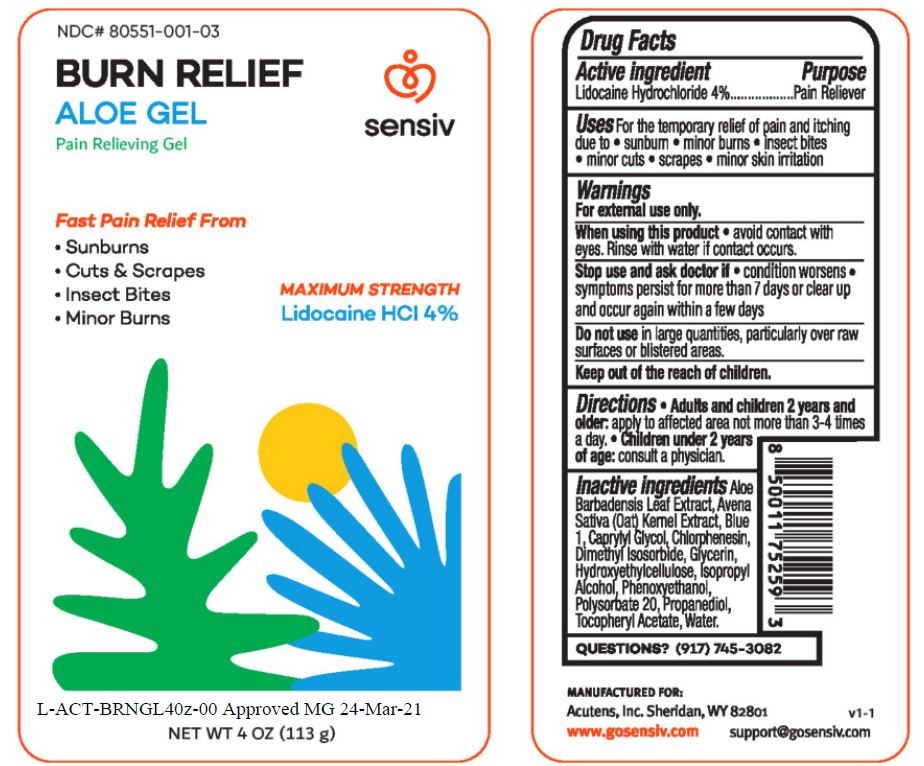 DRUG LABEL: Burn Relief Aloe
NDC: 80551-001 | Form: GEL
Manufacturer: Acutens
Category: otc | Type: HUMAN OTC DRUG LABEL
Date: 20260108

ACTIVE INGREDIENTS: LIDOCAINE HYDROCHLORIDE 4 g/100 g
INACTIVE INGREDIENTS: ALOE; OAT; CAPRYLYL GLYCOL; CHLORPHENESIN; DIMETHYL ISOSORBIDE; GLYCERIN; CETYL HYDROXYETHYLCELLULOSE (350000 MW); ISOPROPYL ALCOHOL; PHENOXYETHANOL; POLYSORBATE 20; PROPANEDIOL; .ALPHA.-TOCOPHEROL ACETATE; WATER

Acutens - Burn Relief Aloe Gel (80551-001)

Active ingredients Purpose

LIDOCAINE HYDROCHLORIDE Pain Reliever

Uses:

For temporary relief of pain and itching due to • sunburn • minor burns • insect bites • minor cuts • scrapes • minor skin irritation

Warnings For external use only

When using this product• Avoid contact with eyes. Rinse with water if contact occurs.

Stop use and ask doctor if• symptoms persist for more than 7 days or clear up and occur again within a few days.

Do not usein large quantities, particularly over raw surfaces or blistered area

Direction

adults and children over 2 years and older: • Apply to affected area not more than 3-4 times a day

• Children under 2 years old: consult a doctor

Inactive ingredients

Aloe Barbadensis Leaf Extract
Avena Sativa (Oat) Kernel Extract
Blue 1
Caprylyl Glycol
Chlorphenesin
Dimethyl Isosorbide
Glycerin
Hydroxyethylcellulose
Isopropyl Alcohol
Phenoxyethanol
Polysorbate 20
Propanediol
Tocopheryl Acetate
Water